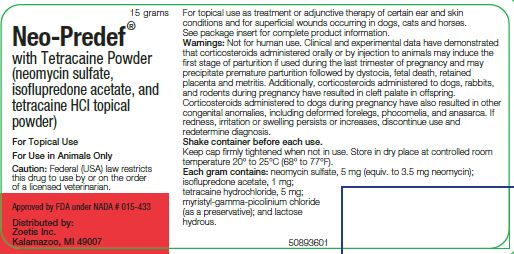 DRUG LABEL: Neo-Predef
NDC: 54771-1584 | Form: POWDER
Manufacturer: Zoetis Inc.
Category: animal | Type: PRESCRIPTION ANIMAL DRUG LABEL
Date: 20200528

ACTIVE INGREDIENTS: NEOMYCIN SULFATE 5 mg/1 g; ISOFLUPREDONE ACETATE 1 mg/1 g; TETRACAINE HYDROCHLORIDE 5 mg/1 g
INACTIVE INGREDIENTS: LACTOSE MONOHYDRATE

Neo-Predef® with Tetracaine Powder

(neomycin sulfate, isoflupredone acetate, and tetracaine hydrochloride topical powder)
For Use in Animals Only
For topical ear and skin use in dogs, cats and horses

Caution

Federal (USA) law restricts this drug to use by or on the order of a licensed veterinarian.

DESCRIPTION

NEO-PREDEF with Tetracaine Powder contains in each gram neomycin sulfate, 5 mg (equivalent to 3.5 mg neomycin); isoflupredone acetate, 1 mg; tetracaine hydrochloride, 5 mg; myristyl-gamma-picolinium chloride (as a preservative); and lactose hydrous. Because of the prompt, potent, and specific actions of the individual components, this combination is well suited for the treatment of certain ear and skin conditions occurring in dogs, cats and horses.

ADVANTAGES OF NEO-PREDEF WITH TETRACAINE

1. Highly potent anti-inflammatory effect of isoflupredone acetate.
2. Wide-spectrum bactericidal effect of neomycin.
3. Rapid anesthetic effect of tetracaine.
4. Prompt relief of symptoms.
5. Reduces further self-inflicted trauma.
6. Ease of application.
7. Adherent to moist surfaces.

ISOFLUPREDONE ACETATE

Isoflupredone acetate markedly inhibits inflammatory reaction through its controlling influence on connective tissue and vascular components. Topically applied isoflupredone acetate is usually rapidly effective. In otitis externa, wounds of the concha, ulcerations of the ear flaps, and irritated lesions of the skin, the inflammatory response may also be effectively inhibited by isoflupredone acetate. Chronic conditions respond more slowly and relapses are more frequent.

NEOMYCIN

Neomycin is an antibiotic substance derived from cultures of the soil organism Streptomyces fradiae. Its antimicrobial range includes both gram-positive and gram-negative organisms commonly responsible for or associated with otic infections, such as staphylococci, streptococci, Escherichia coli., Aerobacter aerogenes, and many strains of Proteus and Pseudomonas organisms. It is not active against fungi. Neomycin is unusually nontoxic for epithelial cells in tissue culture and is nonirritating in therapeutic concentrations. The presence of neomycin in NEO-PREDEF with Tetracaine Powder affords control of neomycin-sensitive organisms.

TETRACAINE

Tetracaine hydrochloride is a topical anesthetic agent that is more potent than either procaine or cocaine in comparable concentration. The duration of anesthetic action of tetracaine exceeds that produced by either butacaine or phenacaine.

Many investigators have demonstrated that local anesthesia plays a significant part in the promotion of healing, especially where pain is a prominent factor. It is believed that trauma stimulates local pain receptors, which results in reflex vasodilation, edema, tenderness, and muscular spasm.

If the reflex is abolished through use of a local anesthetic such as tetracaine, amelioration of these tissue changes that interfere with healing is favored. The local anesthetic action of tetracaine has proved to be of great value in alleviating the pain reflex in painful skin and ear conditions.

INDICATIONS

NEO-PREDEF with Tetracaine Powder is indicated in the treatment or adjunctive therapy of certain ear and skin conditions in dogs, cats and horses caused by or associated with neomycin-susceptible organisms and/or allergy. In addition, it is indicated as superficial dressing applied to minor cuts, wounds, lacerations, abrasions, and for post-surgical application where reduction of pain and inflammatory response is deemed desirable. NEO-PREDEF with Tetracaine Powder may be used as a dusting powder following amputation of tails, claws, and dew-claws; following ear trimming and castrating; and following such surgical procedure as ovariohysterectomies.

Applied superficially, it has been used successfully in the treatment of acute otitis externa in dogs, acute moist dermatitis and interdigital dermatitis in the dog, and as a dusting powder to various minor cuts, lacerations, and abrasions in the horse, cat and dog.

WARNINGS

Not for human use. Do not use in horses intended for human consumption.

Clinical and experimental data have demonstrated that corticosteroids administered orally or by injection to animals may induce the first stage of parturition if used during the last trimester of pregnancy and may precipitate premature parturition followed by dystocia, fetal death, retained placenta and metritis.

Additionally, corticosteroids administered to dogs, rabbits, and rodents during pregnancy have resulted in cleft palate in offspring. Corticosteroids administered to dogs during pregnancy have also resulted in other congenital anomalies, including deformed forelegs, phocomelia, and anasarca.

PRECAUTIONS

Before instilling any medication into the ear, examine the external ear canal thoroughly to be certain the tympanic membrane is not ruptured in order to avoid the possibility of transmitting infection to the middle ear as well as damaging the cochlea or vestibular apparatus from prolonged contact. If hearing or vestibular dysfunction is noted during the course of treatment discontinue use of NEO-PREDEF with Tetracaine Powder.

Incomplete response or exacerbation of corticosteroid-response lesions may be due to the presence of nonsusceptible organisms or to prolonged use of antibiotic-containing preparations resulting in overgrowth of nonsusceptible organisms, particularly Monilia. Thus, if improvement is not noted within two or three days, or if redness, irritation, or swelling persists or increases, the diagnosis should be redetermined and appropriate therapeutic measures initiated.

APPLICATION

After cleansing the affected area, NEO-PREDEF with Tetracaine Powder is applied by compressing the sides of the container with short, sharp squeezes. In most instances a single daily application will be sufficient; however, it may be applied one to three times daily, as required.

HOW SUPPLIED

NEO-PREDEF with Tetracaine Powder is available in 15 gram plastic insufflator bottles. Because of the hygroscopic properties of neomycin sulfate, this bottle should be stored in a dry place. The cap should be replaced when the bottle is not in use. This puffer bottle has been designed to permit dusting when held in any position. Protecting the outlet from moisture will aid in assuring proper function; therefore, the tip should not be allowed to come in contact with moist membranes or weeping surfaces.

STORAGE

Store in a dry place at controlled room temperature 20° to 25°C (68° to 77°F).

Approved by FDA under NADA # 015-433
Distributed by:
Zoetis Inc.
Kalamazoo, MI 49007
Revised: May 2019
50893401